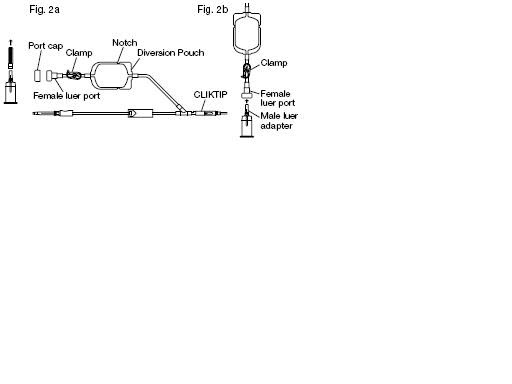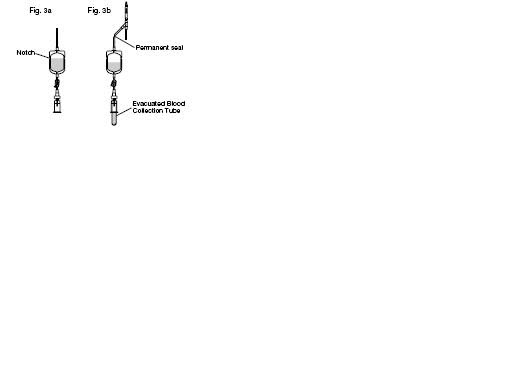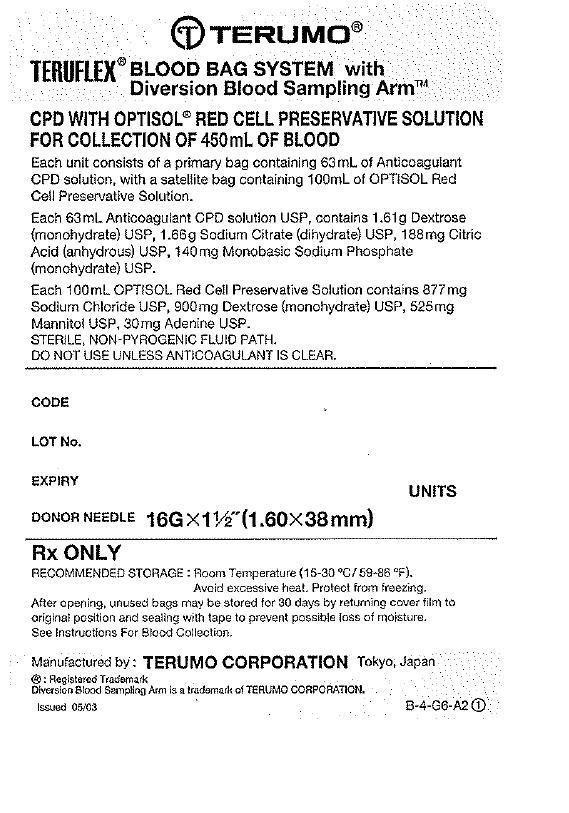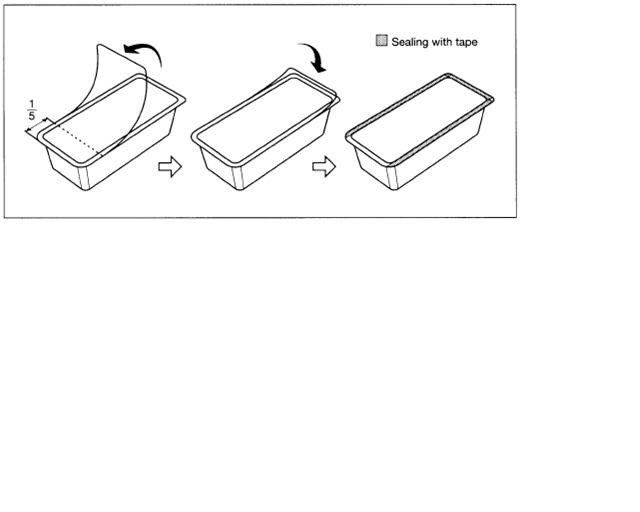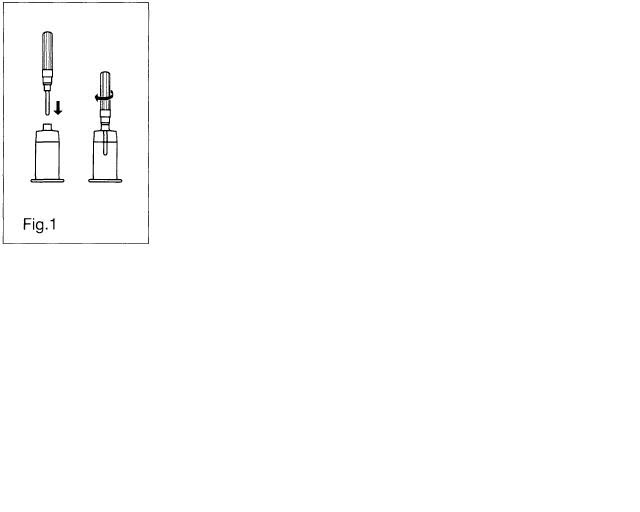 DRUG LABEL: TERUFLEX Blood Bag System with Diversion Blood Sampling Arm Anticoagulant Citrate Phosphate Dextrose (CPD) AND OPTISOL (AS-5) Red Cell Preservative
NDC: 53877-008 | Form: KIT | Route: INTRAVENOUS
Manufacturer: Terumo Corporation
Category: prescription | Type: HUMAN PRESCRIPTION DRUG LABEL
Date: 20181206

ACTIVE INGREDIENTS: Trisodium Citrate Dihydrate 26.3 g/1000 mL; SODIUM PHOSPHATE, MONOBASIC, UNSPECIFIED FORM 2.22 g/1000 mL; Dextrose Monohydrate 25.5 g/1000 mL; Anhydrous Citric Acid 2.99 g/1000 mL; Sodium Chloride 877 mg/100 mL; Dextrose Monohydrate 900 mg/100 mL; Mannitol 525 mg/100 mL; Adenine 30 mg/100 mL
INACTIVE INGREDIENTS: Water; Water

TERUFLEX® BLOOD BAG SYSTEM WITH DIVERSION BLOOD SAMPLING ARM® CPD/OPTISOL® SOLUTION

INDICATIONS AND USAGE

Issued 6/03
TERUFLEX® BLOOD BAG SYSTEM With DIVERSION BLOOD SAMPLING ARM® CPD/OPTISOL® SOLUTION
Read these instructions carefully before use. Rx ONLY.
The Diversion Blood Sampling Arm™ is intended to divert and collect blood for obtaining donor test samples.
• For single use only. Sterile and non-pyrogenic fluid path. Sterilized by steam.
• Intended for the collection, processing and preservation of human blood and components.
PRECAUTIONS
• Do not use unless the solutions are clear.
• Avoid excessive heat and direct sunlight. Protect from freezing.
• Recommended storage conditions: Room Temperature (15-30°C/59-86°F).
• The blood bag configuration is specified on the blister pack label.
CAUTION Do not use a dielectric tube sealer to seal the tubing while the needle is connected to the donor's body unless it is approved for such a purpose.
INSTRUCTIONS FOR BLOOD COLLECTION: Use aseptic technique
Materials Needed:
VENOJECT® ll Tube Holder (code P-1316R) or equivalent
VENOJECT® ll Multi-Sample Luer Adapter (code MN *2000T) or equivalent
Evacuated Blood Collection Tubes (glass or plastic)
1. Prepare the blood bag following your institution's standard operating procedures.
2. If applicable, make a loose knot in the donor tubing below the "Y" and CLIKTIP™ (inline closure device) unless alternate methods are used to seal the tubing at the end of collection.
3. Temporarily clamp the donor tubing between the phlebotomy needle and the "Y".
4. Close the White Clamp below the diversion pouch.
5. Tube Holder/Luer Adapter Assembly:
a) Connect the VENOJECT II Multi-Sample Luer Adapter to the VENOJECT II Tube Holder (or equivalent) (Fig.1).
Insert Fig. 1 here

b) Twist and snap to remove the blue port cap at the end of the Diversion Blood sampling Arm (Fig. 2a).
c) Connect the multi-sample luer adapter to the female luer port. (Fig. 2b)
NOTE: Alternatively, steps a, b and c (above) may be performed at any time during bag preparation or after the blood is collected into the diversion pouch.
Insert Fig. 2a and 2b here

6. Suspend the collection bag as far as possible below the donor's arm.
7. Apply blood pressure cuff or tourniquet to donor's arm. Disinfect site of phlebotomy. If blood pressure cuff is used, inflate to approximately 60 mmHg.
8. Remove the needle cover and perform phlebotomy. Remove the temporary clamp on the donor tubing to permit blood flow into the Diversion Blood Sampling Arm pouch.
CAUTION Do not touch the needle after removing the needle protector. Assure that the White Clamp below the pouch is closed prior to initiating phlebotomy.
9. If using a needle safety device, follow the manufacturer's instructions to secure the device in place.
10. Appropriately secure donor tubing to donor's arm.
11. Position the diversion pouch with the notches up and the Tube Holder/Luer Adapter assembly (or port cap) down. When the level of blood in the pouch is approximately in line
with the notches, the diversion pouch is full. (Fig. 3a)
NOTE: The approximate fill volume of the pouch at the notches is 35 mL.
12. Permanently seal the tubing between the "Y" and the diversion pouch to maintain a closed system using an aluminum clip or a tube sealer approved for use with tubing connected to a donor. (Fig. 3b)
13. To initiate blood flow into the collection bag, break the CLlKTIP between the "Y" and the primary bag.
14. To avoid clot formation, collect samples as soon as possible from the diversion pouch as follows (Fig. 3b)
CAUTION Do not collect donor test samples until the tubing between the "Y" and the diversion pouch is permanently sealed.
a) Open the White Clamp on the tubing below the pouch to open the pathway for sampling.
b) Position the diversion pouch with the notches up and the Tube Holder/Luer Adapter assembly down. Assure that any air in the pouch is at the top and will not enter the
blood collection tubes.
c) Insert vacuum blood collection tube firmly into the tube holder; when full, remove sample tube from holder. Repeat to collect additional samples.
NOTE: The pouch may be removed after the donor test samples are collected. A second seal must be made between the diversion pouch and the permanent seal
prior to removing the pouch.
Insert Fig. 3a and 3b here

15. Once samples are obtained, mix blood with anticoagulant in the primary bag and continue to mix at several intervals during collection.
16. Collect labeled volume of blood (+/–10%).
17. When the desired amount of blood has been collected, seal the tubing or tighten the loose knot (white knot) prepared in step 2. Make a second seal between the first seal or knot and
the CLlKTIP below the "Y". Various methods may be used to seal tubing.
18. Release pressure on the donor's arm and remove the needle. If using a needle safety device, follow the manufacturer's instructions to remove the needle. Sever the donor tubing between the two seals previously made below the CLlKTIP and "Y".
CAUTION Discard the Diversion Blood Sampling Arm and phlebotomy needle/donor tubing according to institutional procedures.
19. Immediately after collection, invert the bag several times to assure blood and anticoagulant are well mixed.
20. Strip blood from the donor tubing into the bag, mix well, and allow tubing to refill. Seal on or near the X marks on the donor tubing to provide numbered aliquots of anticoagulated blood for testing.
21. The time of addition of OPTISOL Solution may vary depending on the processing option selected. Add the solution under one of the following conditions after removal of plasma:
a) Within 8 hours of whole blood collection, if components are prepared.
b) Within 72 hours of collection if whole blood is refrigerated immediately following collection.
22. Centrifuge the unit to separate red cells from plasma.
23. Break the CLlKTIP of primary collection bag and transfer the plasma into the satellite bag. Clamp transfer tubing of satellite bag.
24. Break the CLlKTIP of OPTlSOL Solution bag and drain contents into primary bag containing red blood cells. Seal tubing of primary bag in two places, and cut between seals
and separate from satellite bag(s).
NOTE: For TERUFLEX double bags, seal OPTISOL Solution bag tubing in two places and cut between seals. Discard OPTISOL Solution container.
25. Invert the red cell- OPTISOL mixture several times to insure the final AS-5 red cell product is well suspended.
26. Store AS-5 Red Blood Cells between 1-6°C.
27. Infuse AS-5 Red Blood Cells within 42 days of collection.
For further processing, use standard component processing techniques.
To open blister package, peel cover film back four fifths of its length.
After opening, unused bags may be stored for 30 days by returning cover film to original position and sealing with tape to prevent possible loss of moisture.
Insert Fig. 4 here

CAUTIONS
•The packet of AGELESS contained in this package absorbs oxygen and generates heat on removal. Handle it with care.
• Dispose with packet in tray.
• Do not dispose with wastes containing volatile or flammable materials.
• Discard AGELESS packet without opening.
N-BB-OP-A2(DB) 1
TERUMO® MANUFACTURED BY: TERUMO CORPORATION 44-1, 2-CHOME, HATAGAYA, SHIBUYA-KU, TOKYO, JAPAN MADE IN JAPAN
®: Registered Trademark Diversion Blood Sampling Arm and CLIKTIP are trademarks of TERUMO CORPORATION.
© TERUMO CORPORATION 2003 03F10

Tray/Case Label

TERUFLEX® BLOOD BAG SYSTEM with
DIVERSION BLOOD SAMPLING ARM®
CPD WITH OPTISOL® RED CELL PRESERVATIVE SOLUTION
FOR COLLECTION OF 450mL OF BLOOD
Each unit consists of a collection bag containing 63mL of Anticoagulant
CPD solution, with a satellite bag containing 100mL of OPTlSOL Red
Cell Preservative Solution.
Each 63mL Anticoagulant CPD solution USP contains 1.61g Dextrose
(monohydrate) USP, 1.66g Sodium Citrate (dihydrate) USP, 188mg Citric
Acid (anhydrous) USP, 140mg Monobasic Sodium Phosphate
(monohydrate) USP.
Each 100mL OPTISOL Red Cell Preservative Solution contains 877mg
Sodium Chloride USP, 900mg Dextrose (monohydrate) USP, 525mg
Mannitol USP, 30mg Adenine USP.
STERILE, NON-PYROGENIC FLUID PATH.
DO NOT USE UNLESS ANTICOAGULANT IS CLEAR.
CODE
LOT No.
EXPIRY
UNITS
DONOR NEEDLE 16G x 1 1/2˝ (1.60 x 38mm)
Rx ONLY
RECOMMENDED STORAGE: Room Temperature (15-30°C/59-86°F).
Avoid excessive heat. Protect from freezing.
After opening, unused bags may be stored for 30 days by returning cover film to original
position and sealing with tape to prevent possible loss of moisture.
See Instructions For Blood Collection.
Manufactured by : TERUMO CORPORATION Tokyo, Japan
® : Registered Trademark
Diversion Blood Sampling Arm is a trademark of TERUMO CORPORATION.
Issued 05/03
B-4-G6-A2 1
Place Label here